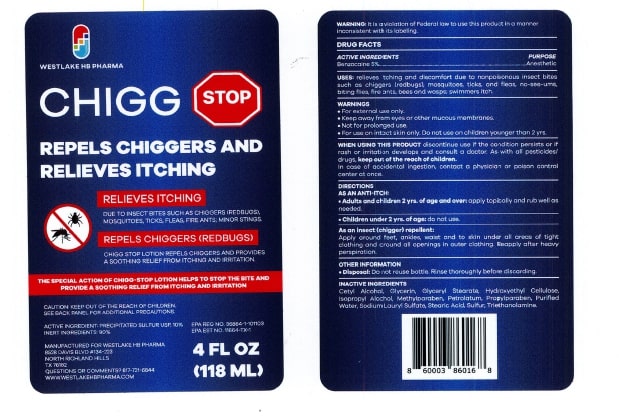 DRUG LABEL: Chigg Away
NDC: 82895-857 | Form: LOTION
Manufacturer: Westlake HB Pharma LLC
Category: otc | Type: HUMAN OTC DRUG LABEL
Date: 20250724

ACTIVE INGREDIENTS: BENZOCAINE 50 mg/1 mL
INACTIVE INGREDIENTS: CETYL ALCOHOL; GLYCERIN; GLYCERYL MONOSTEARATE; ISOPROPYL ALCOHOL; METHYLPARABEN; PETROLATUM; PROPYLPARABEN; WATER; SODIUM LAURYL SULFATE; STEARIC ACID; SULFUR; TROLAMINE; HYDROXYETHYL CELLULOSE (1500 MPA.S AT 1%)

Chigg Stop

Chigg Away

Drug Facts

Active Ingredient

Benzocaine 5%

Purpose

Anesthetic

Uses

Relieves itching and discomfort due to nonpoisonous insect bites such as chiggers (redbugs), mosquitoes, ticks, and fleas, no-see-ums, biting flies, fire ants, bees and wasps; swimmers itch.

Warnings

For external use only.

Keep away from eyes or other mucous membranes. Not for prolonged use. For use on intact skin only. Do not use on children younger than 2 yrs.

When using this product

discontinue use if the condition persists or if rash or irritation develops and consult a doctor. As with all pesticides/drugs,

keep out of reach of children.

In case of accidental ingestion, contact a physician or poison control center at once.

Directions

- As an anti-itch: Adults and children 2 yrs. of age and over: apply topically and rub well as needed. Children under 2 years of age: Do not use.
- As an insect (chigger) repellent: Apply around feet, ankles, waist and to skin under all areas of tight clothing and around all openings in outer clothing. Reapply after heavy respiration.

Other Information

- Disposal: Do not reuse bottle. Rinse thoroughly before discarding.

Inactive Ingredient

Cetyl Alcohol, Glycerin, Glyceryl Stearate, Hydroxyethyl Cellulose, Isopropyl Alcohol, Methylparaben, Petrolatum, Propylparaben, Purified Water, Sodium Lauryl Sulfate, Stearic Acid, Sulfur, Triethanolamine..

PRINCIPAL DISPLAY PANEL

NDC 86000-857-05
CHIGG
STOP
RELIEVES ITCHING
REPELS CHIGGERS
4 FL OZ
(118 ML)